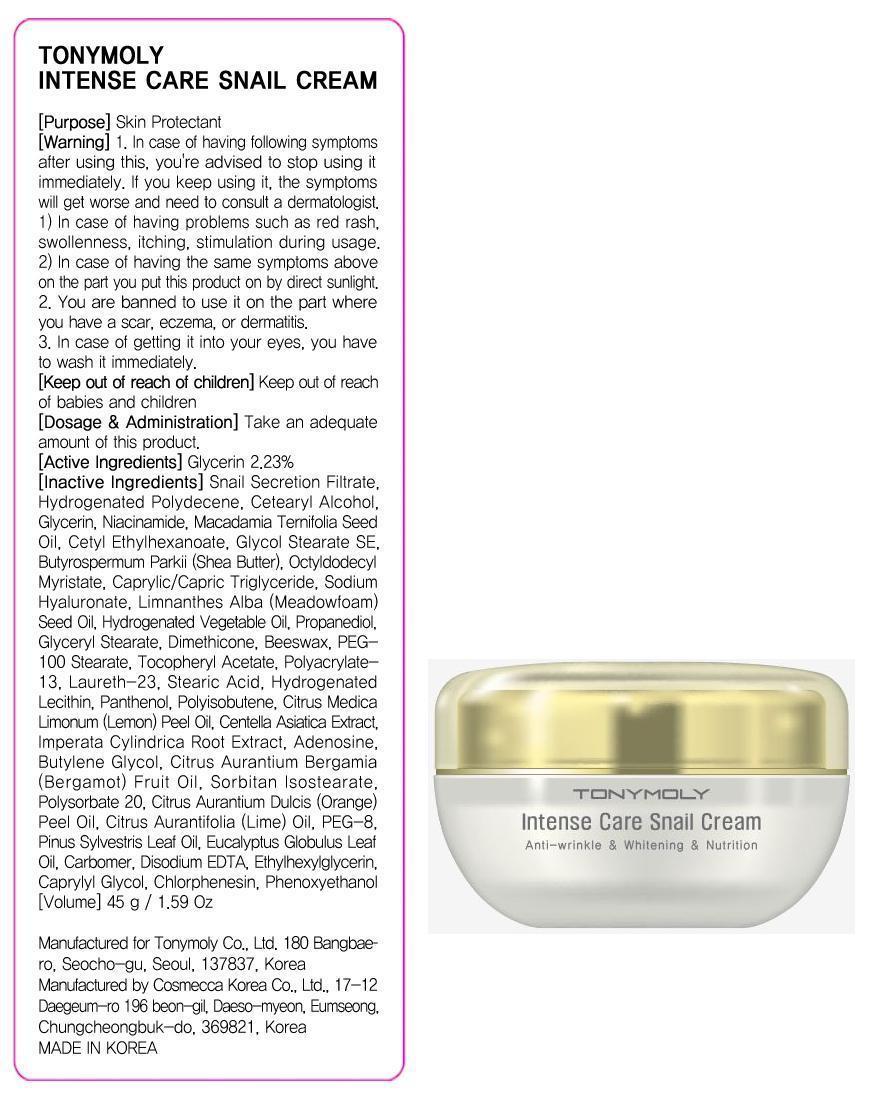 DRUG LABEL: TONYMOLY INTENSE CARE SNAIL
NDC: 59078-054 | Form: CREAM
Manufacturer: TONYMOLY CO., LTD.
Category: otc | Type: HUMAN OTC DRUG LABEL
Date: 20150326

ACTIVE INGREDIENTS: Glycerin 1.0 g/45 g
INACTIVE INGREDIENTS: Niacinamide; SHEA BUTTER

ACTIVE INGREDIENT

Active Ingredient: Glycerin 2.23%

INACTIVE INGREDIENT

Inactive Ingredients: Snail Secretion Filtrate, Hydrogenated Polydecene, Cetearyl Alcohol, Niacinamide, Macadamia Ternifolia Seed Oil, Cetyl Ethylhexanoate, Glycol Stearate SE, Butyrospermum Parkii (Shea Butter), Octyldodecyl Myristate, Caprylic/Capric Triglyceride, Sodium Hyaluronate, Limnanthes Alba (Meadowfoam) Seed Oil, Hydrogenated Vegetable Oil, Propanediol, Glyceryl Stearate, Dimethicone, Beeswax, PEG-100 Stearate, Tocopheryl Acetate, Polyacrylate-13, Laureth-23, Stearic Acid, Hydrogenated Lecithin, Panthenol, Polyisobutene, Citrus Medica Limonum (Lemon) Peel Oil, Centella Asiatica Extract, Imperata Cylindrica Root Extract, Adenosine, Butylene Glycol, Citrus Aurantium Bergamia (Bergamot) Fruit Oil, Sorbitan Isostearate, Polysorbate 20, Citrus Aurantium Dulcis (Orange) Peel Oil, Citrus Aurantifolia (Lime) Oil, PEG-8, Pinus Sylvestris Leaf Oil, Eucalyptus Globulus Leaf Oil, Carbomer, Disodium EDTA, Ethylhexylglycerin, Caprylyl Glycol, Chlorphenesin, Phenoxyethanol

PURPOSE

Purpose: Skin Protectant

WARNINGS

Warnings: 1. In case of having following symptoms after using this, you're advised to stop using it immediately. If you keep using it, the symptoms will get worse and need to consult a dermatologist. 1) In case of having problems such as red rash, swollenness, itching, stimulation during usage. 2) In case of having the same symptoms above on the part you put this product on by direct sunlight. 2. You are banned to use it on the part where you have a scar, eczema, or dermatitis. 3. In case of getting it into your eyes, you have to wash it immediately.

Keep out of reach of Children: Keep out of reach of babies and children

INDICATIONS & USAGE

Indication & Usage: After using eye cream, apply a pea sized amount evenly distribute across the face. Gently pat for better absorption.

DOSAGE & ADMINISTRATION

Dosage & Administration: Take an adequate amount of this product.